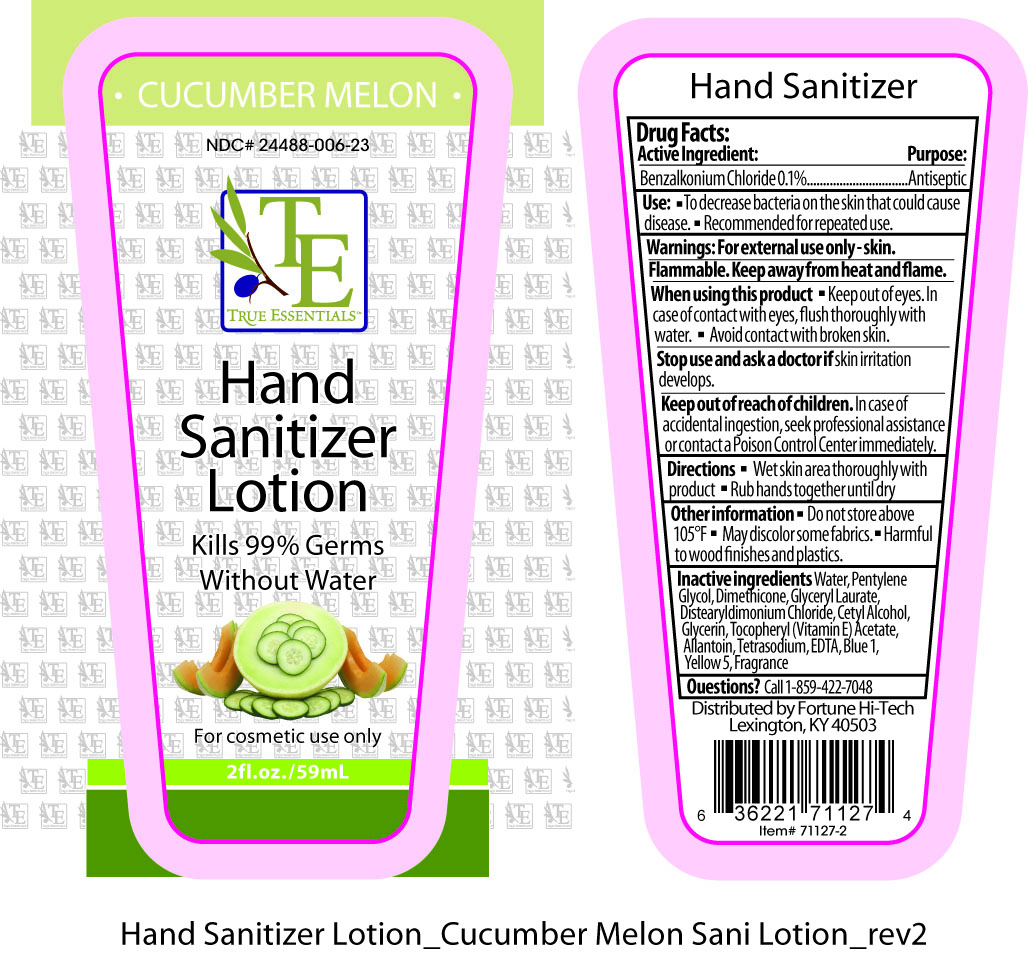 DRUG LABEL: True Essentials
NDC: 24488-006 | Form: LOTION
Manufacturer: Fortune Hi-Tech
Category: otc | Type: HUMAN OTC DRUG LABEL
Date: 20110413

ACTIVE INGREDIENTS: BENZALKONIUM CHLORIDE .59 mL/59 mL
INACTIVE INGREDIENTS: WATER; PENTYLENE GLYCOL; DIMETHICONE; GLYCERYL LAURATE; DISTEARYLDIMONIUM CHLORIDE; CETYL ALCOHOL; GLYCERIN; ALPHA-TOCOPHEROL ACETATE; ALLANTOIN; EDETATE SODIUM; FD&C BLUE NO. 1; FD&C YELLOW NO. 5

Drug Facts:

Active Ingredient:........................Purpose:

Benzalkonium Chloride 0.1%........................Antiseptic

Use:

- To decrease bacteria on the skin that could cause disease.
- Recommended for repeated use.

Warnings:

For external use only--skin.

Flammable.

Keep away from heat and flame.

When using this product

- Keep out of eyes. In case of contact with eyes, flush thoroughly with water.
- Avoid contact with broken skin.

Stop use and ask a doctor if

skin irritation develops.

Keep out of reach of children.

In case of accidental ingestion, seek professional assistance or contact a Poison Control Center immediately.

Directions

- Wet skin area thoroughly with product
- Rub hands together until dry

Other information

- Do not store above 105°,
- May discolor some fabrics,
- Harmful to wood finishes and plastics.

Inactive ingredients

Water, Pentylene Glycol, Dimethicone, Glyceryl Laurate, Distearyldimonium Chloride, Cetyl Alcohol, Glycerin, Tocopheryl (Vitamin E) Acetate, Allantoin, Tetrasodium EDTA, Blue 1, Yellow 5, Fragrance

Questions?

Call 1-859-422-7048

PACKAGE LABEL

Placeholder Text